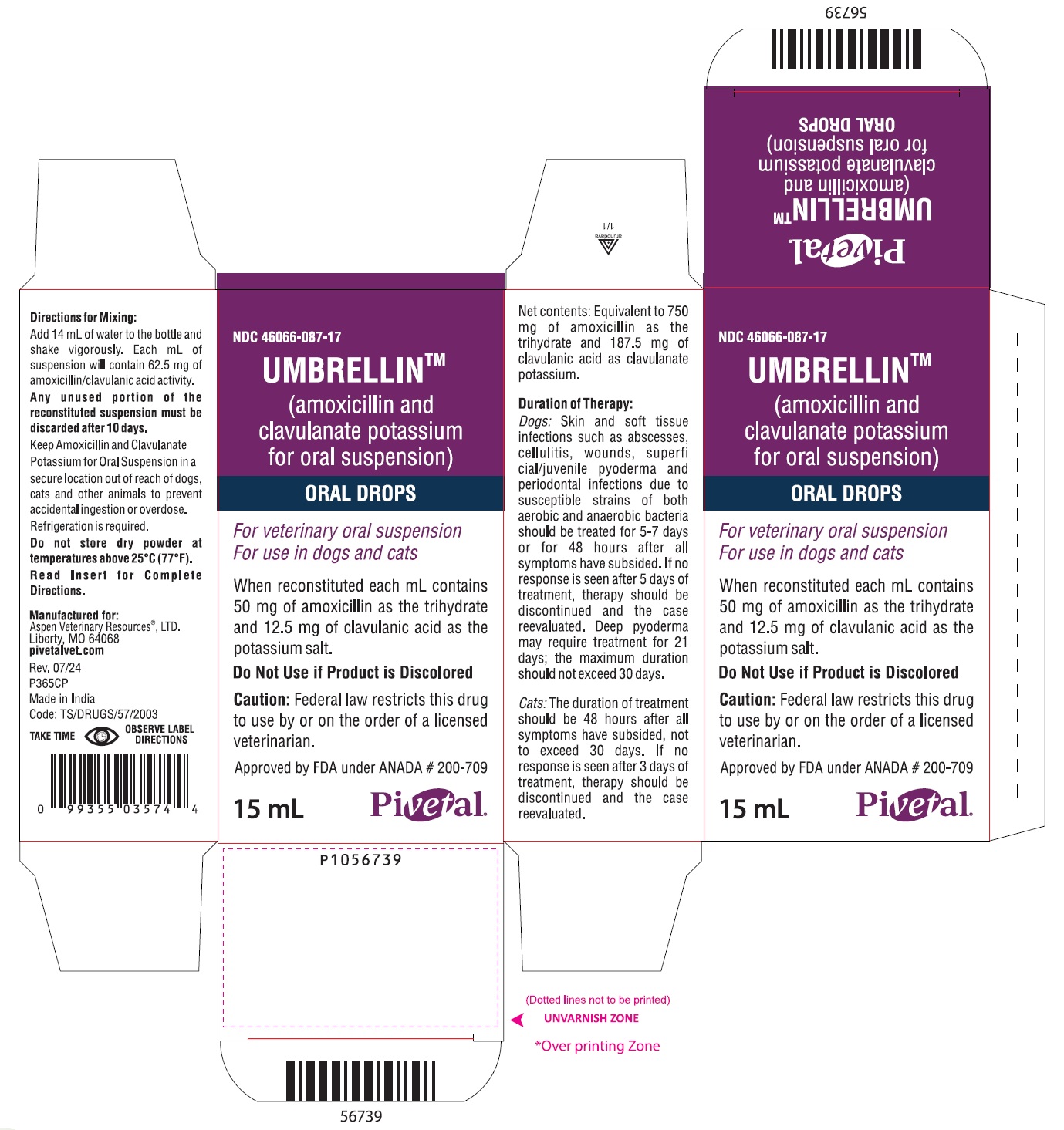 DRUG LABEL: Umbrellin
NDC: 46066-087 | Form: SUSPENSION
Manufacturer: Aspen Veterinary Resources Ltd
Category: animal | Type: PRESCRIPTION ANIMAL DRUG LABEL
Date: 20250409

ACTIVE INGREDIENTS: AMOXICILLIN ANHYDROUS 50 mg/1 mL; CLAVULANATE POTASSIUM 12.5 mg/1 mL

UmbrellinTM
(amoxicillin and clavulanate potassium for oral suspension)
ORAL DROPS

For veterinary oral suspension
For use in dogs and cats

CAUTION

Federal law restricts this drug to use by or on the order of a licensed veterinarian.

DESCRIPTION

Umbrellin™ Drops is an orally administered formulation comprised of the broad-spectrum antibiotic amoxicillin trihydrate and the β-lactamase inhibitor, clavulanate potassium (the potassium salt of clavulanic acid).

Amoxicillin trihydrate is a semisynthetic antibiotic with a broad spectrum of bactericidal activity against many gram-positive and gram-negative, aerobic and anaerobic microorganisms. It does not resist destruction by β-lactamases; therefore, it is not effective against β-lactamase-producing bacteria. Chemically, it is D(-)-α-amino-p-hydroxybenzyl penicillin trihydrate.

Clavulanic acid, an inhibitor of β-lactamase enzymes, is produced by the fermentation of Streptomyces clavuligerus. Clavulanic acid by itself has only weak antibacterial activity. Chemically, clavulanate potassium is potassium z-(3R,5R)-2-β-hydroxyethylidene clavam-3-carboxylate.

CLINICAL PHARMACOLOGY

Umbrellin™ Drops is stable in the presence of gastric acid and is not significantly influenced by gastric or intestinal contents. The 2 components are rapidly absorbed resulting in amoxicillin and clavulanic acid concentrations in serum, urine, and tissues similar to those produced when each is administered alone.

Amoxicillin and clavulanic acid diffuse readily into most body tissues and fluids with the exception of brain and spinal fluid, which amoxicillin penetrates adequately when meninges are inflamed. Most of the amoxicillin is excreted unchanged in the urine. Clavulanic acid’s penetration into spinal fluid is unknown at this time. Approximately 15% of the administered dose of clavulanic acid is excreted in the urine within the first 6 hours.

Umbrellin™ Drops combines the distinctive properties of a broad-spectrum antibiotic and a β-lactamase inhibitor to effectively extend the antibacterial spectrum of amoxicillin to include β-lactamase-producing as well as non-β-lactamase-producing aerobic and anaerobic organisms.

Microbiology
Amoxicillin is bactericidal in action and acts through the inhibition of biosynthesis of cell wall mucopeptide of susceptible organisms. The action of clavulanic acid extends the antimicrobial spectrum of amoxicillin to include organisms resistant to amoxicillin and other β-lactam antibiotics.

Amoxicillin/clavulanate has been shown to have a wide range of activity which includes β-lactamase-producing strains of both gram-positive and gram-negative aerobes, facultative anaerobes, and obligate anaerobes. Many strains of the following organisms, including β-lactamase-producing strains, isolated from veterinary sources, were found to be susceptible to amoxicillin/clavulanate in vitro but the clinical significance of this activity has not been demonstrated for some of these organisms in animals. Aerobic bacteria, including Staphylococcus aureus^1, β-lactamase-producing Staphylococcus aureus^1 (penicillin resistant), Staphylococcus species^1, Staphylococcus epidermidis, Staphylococcus intermedius, Streptococcus faecalis, Streptococcus species^1, Corynebacterium pyogenes, Corynebacterium species, Erysipelothrix rhusiopathiae, Bordetella bronchiseptica, Escherichia coli^1, Proteus mirabilis, Proteus species, Enterobacter species, Klebsiella pneumoniae, Salmonella dublin, Salmonella typhimurium, Pasteurella multocida^1, Pasteurella haemolytica, Pasteurella species^1.

^1The susceptibility of these organisms has also been demonstrated in in vivo studies.

Studies have demonstrated that both aerobic and anaerobic flora are isolated from gingival cultures of dogs with clinical evidence of periodontal disease. Both gram-positive and gram-negative aerobic and anaerobic subgingival isolates indicate sensitivity to amoxicillin/clavulanic acid during antimicrobial susceptibility testing.

Susceptibility test

The recommended quantitative disc susceptibility method (FEDERAL REGISTER 37:20527–29; Bauer AW, Kirby WMM, Sherris JC, et al: Antibiotic susceptibility testing by standardized single disc method. Am J Clin Path 45:493, 1966) utilized 30 mcg Augmentin® (AMC) discs for estimating the susceptibility of bacteria to amoxicillin and clavulanate potassium tablets and amoxicillin and clavulanate potassium for oral suspension.

INDICATIONS AND USAGE

Umbrellin™ Drops are indicated in the treatment of:

Dogs: Skin and soft tissue infections such as wounds, abscesses, cellulitis, superficial/juvenile and deep pyoderma due to susceptible strains of the following organisms: β-lactamase-producing Staphylococcus aureus, non-β-lactamase-producing Staphylococcus aureus, Staphylococcus spp., Streptococcus spp., and E. coli.

Periodontal infections due to susceptible strains of both aerobic and anaerobic bacteria. Umbrellin™ Drops has been shown to be clinically effective for treating cases of canine periodontal disease.

Cats: Skin and soft tissue infections such as wounds, abscesses, and cellulitis/dermatitis due to susceptible strains of the following organisms: β-lactamase-producing Staphylococcus aureus, non-β-lactamase-producing Staphylococcus aureus, Staphylococcus spp., Streptococcus spp., E. coli, Pasteurella multocida, and Pasteurella spp.

Urinary tract infections (cystitis) due to susceptible strains of E. coli.

Therapy may be initiated with Umbrellin™ Drops prior to obtaining results from bacteriological and susceptibility studies.

A culture should be obtained prior to treatment to determine susceptibility of the organisms to Umbrellin™ Drops. Following determination of susceptibility results and clinical response to medication, therapy may be reevaluated.

CONTRAINDICATIONS

The use of this drug is contraindicated in animals with a history of an allergic reaction to any of the penicillins or cephalosporins.

WARNINGS

Safety of use in pregnant or breeding animals has not been determined. For use in dogs and cats only.

Keep Umbrellin™ Drops in a secure location out of reach of dogs, cats and other animals to prevent accidental ingestion or overdose.

ADVERSE REACTIONS

Umbrellin™ Drops contains a semisynthetic penicillin (amoxicillin) and has the potential for producing allergic reactions.

If an allergic reaction occurs, administer epinephrine and/or steroids.

To report suspected adverse drug events, for technical assistance or to obtain a copy of the Safety Data Sheet, contact the manufacturer at 1-844-227-6687. For additional information about adverse experience reporting for animal drugs, contact FDA at 1-888-FDA-VETS or http://www.fda.gov/reportanimalae.

DOSAGE AND ADMINISTRATION

Dogs: The recommended dosage is 6.25 mg/lb (1 mL/10 lb) of body weight twice a day. Skin and soft tissue infections such as abscesses, cellulitis, wounds, superficial/juvenile pyoderma, and periodontal infections should be treated for 5–7 days or for 48 hours after all symptoms have subsided. If no response is seen after 5 days of treatment, therapy should be discontinued and the case reevaluated. Deep pyoderma may require treatment for 21 days; the maximum duration of treatment should not exceed 30 days.

Cats: The recommended dosage is 62.5 mg (1 mL) twice a day. Skin and soft tissue infections such as abscesses and cellulitis/dermatitis should be treated for 5–7 days or 48 hours after all symptoms have subsided, not to exceed 30 days. If no response is seen after 3 days of treatment, therapy should be discontinued and the case reevaluated.

Urinary tract infections may require treatment for 10–14 days or longer. The maximum duration of treatment should not exceed 30 days.

Reconstitution instructions - Oral Suspension
Add 14 mL of water to the 15-mL bottle and shake vigorously. Each mL of suspension will contain 50 mg of amoxicillin activity as the trihydrate and 12.5 mg of clavulanic acid activity as the potassium salt.

Note:
Any unused portion of the reconstituted suspension must be discarded after 10 days.

Refrigeration of the reconstituted suspension is required.

STORAGE CONDITIONS

Do not store dry powder at temperatures above 25°C (77°F).

HOW SUPPLIED

Umbrellin™ Drops are supplied in 15-mL bottles containing 50 mg of amoxicillin/12.5 mg of clavulanic acid per mL.

Approved by FDA under ANADA # 200-709

Augmentin® is a trademark owned by GlaxoSmithKline.

Manufactured for:
Aspen Veterinary Resources®, LTD.
Liberty, MO 64068
pivetalvet.com
Rev. 01/22

Made in India

PACKAGE LABEL.PRINCIPAL DISPLAY PANEL

NDC 46066-087-17

UMBRELLIN™

(amoxicillin and clavulanate potassium for oral suspension)

ORAL DROPS

For veterinary oral suspension

For use in dogs and cats

When reconstituted each mL contains 50 mg of amoxicillin as the trihydrate and 12.5 mg of clavulanic acid as the potassium salt.

Do Not Use if Product is Discolored

Caution: Federal law restricts this drug to use by or on the order of a licensed veterinarian.

Approved by FDA under ANADA # 200-709

15 mL

Pivetal